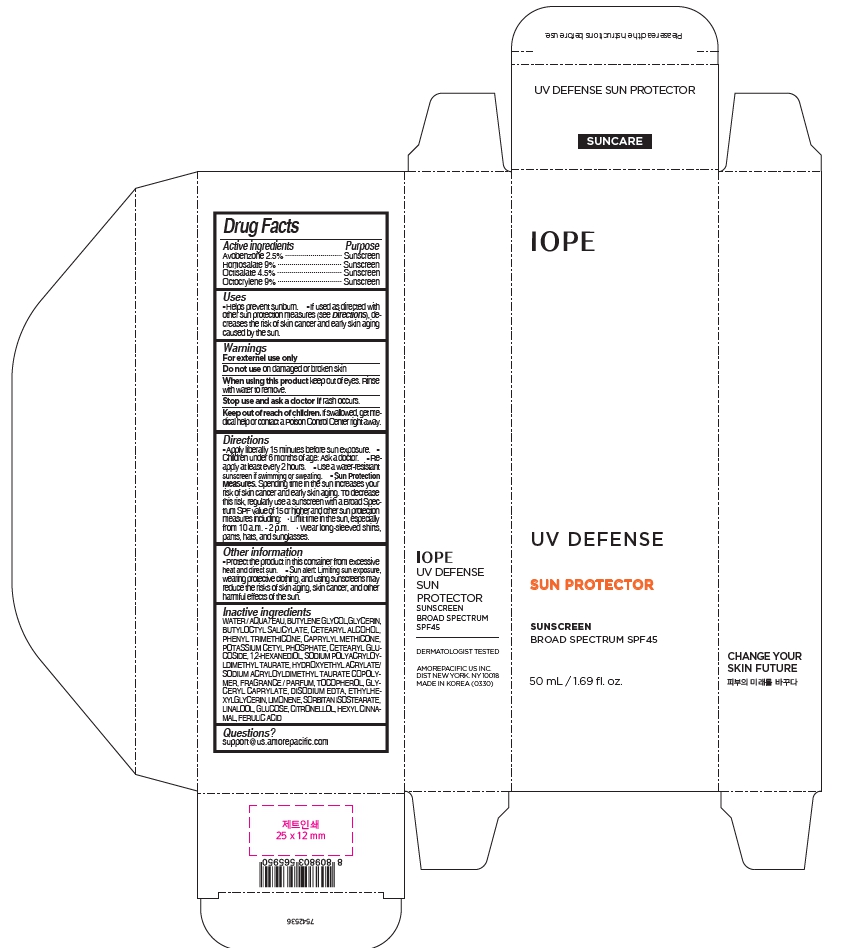 DRUG LABEL: IOPE UV DEFENSE SUN PROTECTOR
NDC: 43419-420 | Form: CREAM
Manufacturer: AMOREPACIFIC CORPORATION
Category: otc | Type: HUMAN OTC DRUG LABEL
Date: 20241008

ACTIVE INGREDIENTS: OCTISALATE 2.25 g/50 mL; OCTOCRYLENE 4.5 g/50 mL; AVOBENZONE 1.25 g/50 mL; HOMOSALATE 4.5 g/50 mL
INACTIVE INGREDIENTS: CETEARYL GLUCOSIDE; SORBITAN ISOSTEARATE; ANHYDROUS DEXTROSE; .BETA.-CITRONELLOL, (R)-; 1,2-HEXANEDIOL; .ALPHA.-HEXYLCINNAMALDEHYDE; PHENYL TRIMETHICONE; CAPRYLYL TRISILOXANE; WATER; POTASSIUM CETYL PHOSPHATE; SODIUM POLYACRYLOYLDIMETHYL TAURATE; HYDROXYETHYL ACRYLATE/SODIUM ACRYLOYLDIMETHYL TAURATE COPOLYMER (45000 MPA.S AT 1%); ETHYLHEXYLGLYCERIN; BUTYLENE GLYCOL; GLYCERIN; BUTYLOCTYL SALICYLATE; TOCOPHEROL; LINALOOL, (+/-)-; EDETATE DISODIUM; CETOSTEARYL ALCOHOL; GLYCERYL CAPRYLATE; LIMONENE, (+)-; FERULIC ACID

IOPE UV DEFENSE SUN PROTECTOR

Active ingredients

Avobenzone 2.5%

Homosalate 9%

Octisalate 4.5%

Octocrylene 9%

Purpose

Sunscreen

Uses

Helps prevent sunburn.

If used as directed with other sun protection measures (see Directions), decreases the risk of skin cancer and early skin aging caused by the sun.

Warnings

For externel use only

Do not use on damaged or broken skin

When using this product keep out of eyes. Rinse with water to remove.

Stop use and ask a doctor if rash occurs.

Keep out of reach of children. If swallowed, get medical help or contact a Poison Control Center right away.

Directions

Apply liberally 15 minutes before sun exposure.

Children under 6 months of age: Ask a doctor.

Reapply at least every 2 hours.

Use a water-resistant sunscreen if swimming or sweating.

Sun Protection Measures. Spending time in the sun increases your risk of skin cancer and early skin aging. To decrease this risk, regularly use a sunscreen with a Broad Spectrum SPF value of 15 or higher and other sun protection

measures including: Limit time in the sun, especially from 10 a.m. - 2 p.m. Wear long-sleeved shirts, pants, hats, and sunglasses.

Other information

Protect the product in this container from excessive heat and direct sun.

Sun alert: Limiting sun exposure, wearing protective clothing, and using sunscreens may reduce the risks of skin aging, skin cancer, and other harmful effects of the sun.

Inactive ingredients

WATER, BUTYLENE GLYCOL,GLYCERIN, BUTYLOCTYL SALICYLATE, CETEARYL ALCOHOL, PHENYL TRIMETHICONE, CAPRYLYL METHICONE, POTASSIUM CETYL PHOSPHATE, CETEARYL GLUCOSIDE, 1,2-HEXANEDIOL, SODIUM POLYACRYLOYLDIMETHYL, TAURATE, HYDROXYETHYL ACRYLATE/SODIUM ACRYLOYLDIMETHYL TAURATE COPOLYMER,
FRAGRANCE / PARFUM, TOCOPHEROL, GLYCERYL CAPRYLATE, DISODIUM EDTA, ETHYLHEXYLGLYCERIN, LIMONENE, SORBITAN ISOSTEARATE, LINALOOL, GLUCOSE, CITRONELLOL, HEXYL CINNAMAL, FERULIC ACID

Questions?

support@us.amorepacific.com

IOPE UV Defense Sun Protector Sunscreen

IOPE

UV DEFENSE

SUN PROTECTOR

SUNSCREEN

BROAD SPECTRUM SPF45

50 mL / 1.69 fl. oz.